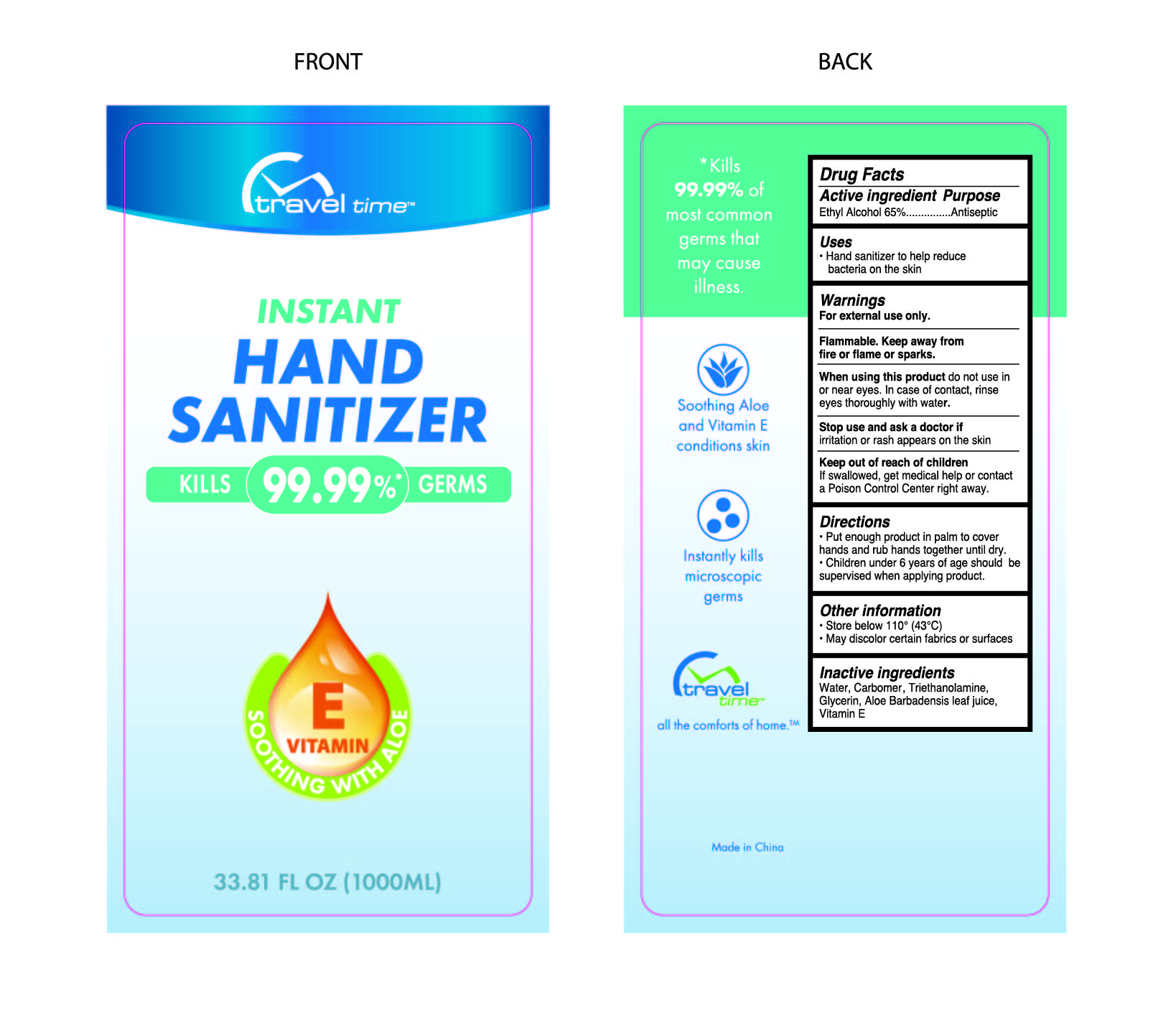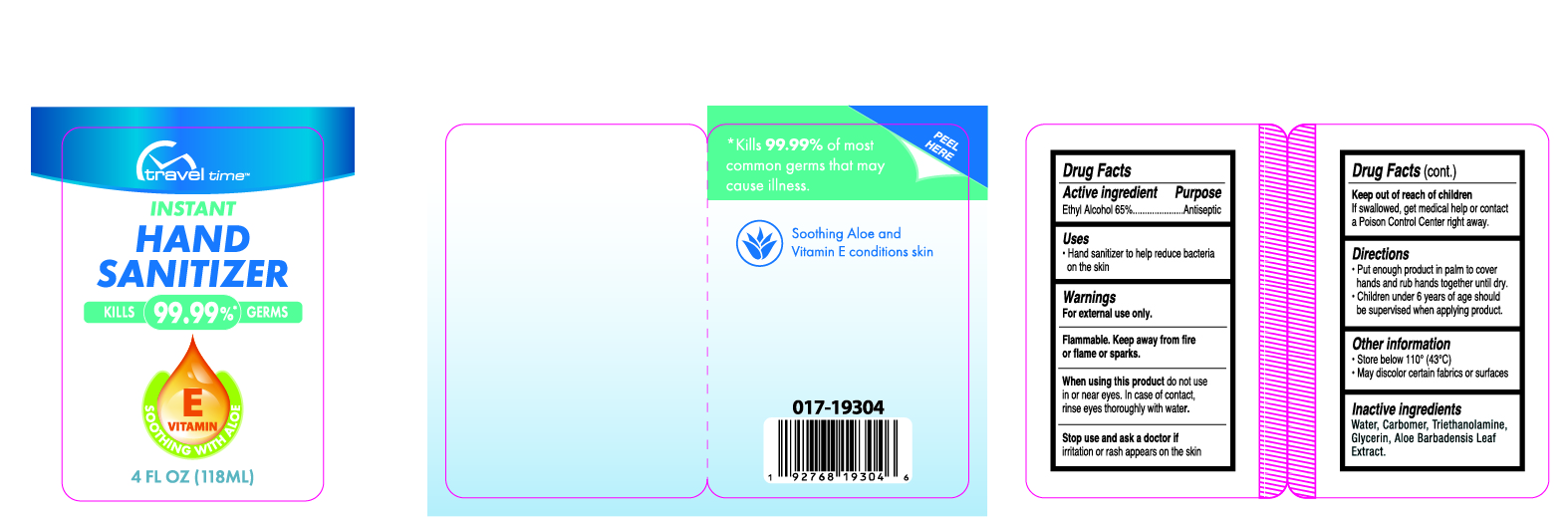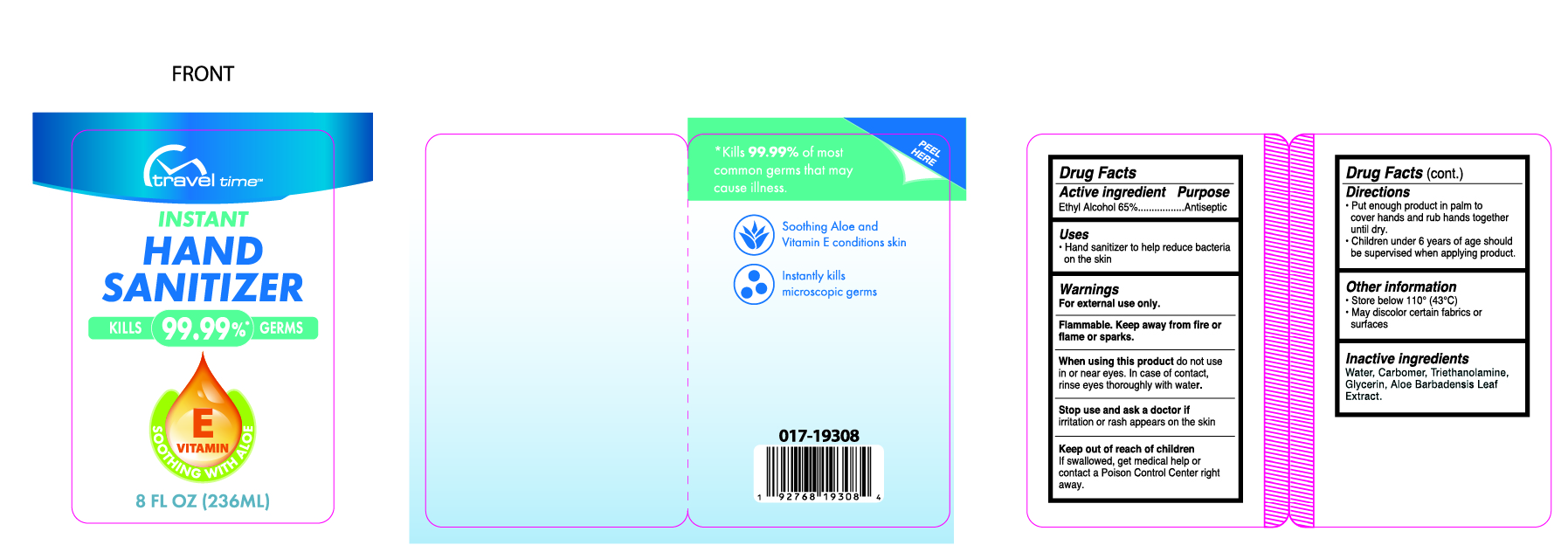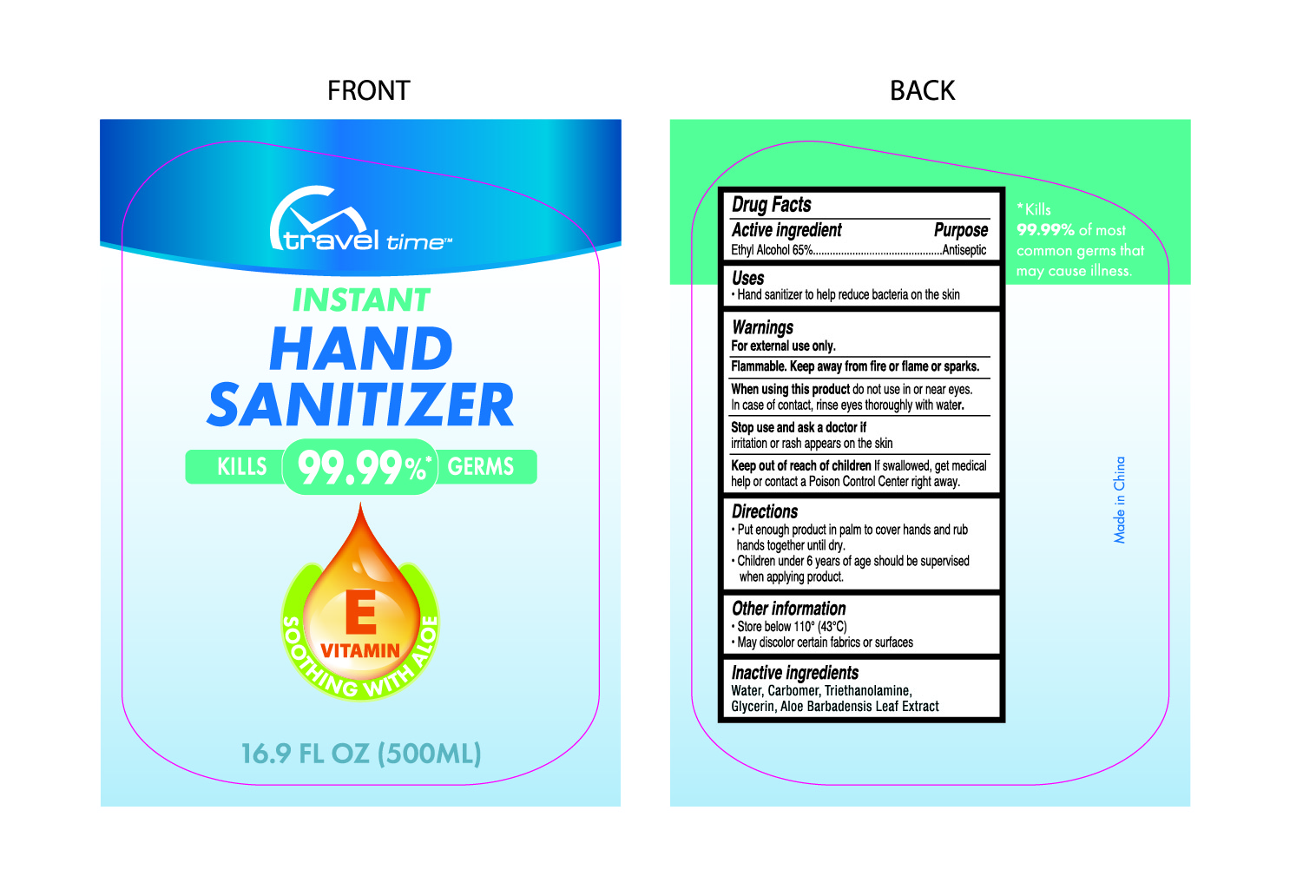 DRUG LABEL: HAND SANITIZER
NDC: 47993-264 | Form: GEL
Manufacturer: NINGBO JIANGBEI OCEAN STAR TRADING CO.,LTD
Category: otc | Type: HUMAN OTC DRUG LABEL
Date: 20201104

ACTIVE INGREDIENTS: ALCOHOL 65 g/112 mL
INACTIVE INGREDIENTS: TRIETHANOLAMINE BENZOATE; CARBOMER 940; WATER; GLYCERIN; ALOE VERA LEAF

47993-264

Active ingredients

Ethyl Alcohol 65%

PURPOSE

Antiseptic

Uses：

Hand sanitizer to help reduce bacteria on the skin.

Warnings:

For external use only.

Flammable. Keep away from fire or flame or sparks.

When using this product do not use in or near eyes. In case of contact，rinse eyes thoroughly with water.

Stop use and ask a doctor if irritation or rash appears on the skin.

Keep out of reach of children. If swallowed，get medical help or contact a Poison Control Center right away.

Directions:

- Put enough product in palm to cover hands and rub hands together until dry.
- Children under 6 years of age should be supervised when applying product.

Other information

- Store below 110℉（43℃）
- May discolor certain fabrics or surface

Inactive Ingredients:

Water,Carbomer,Triethanolamine,Glycerin,Aloe Barbadensis Leaf Extract